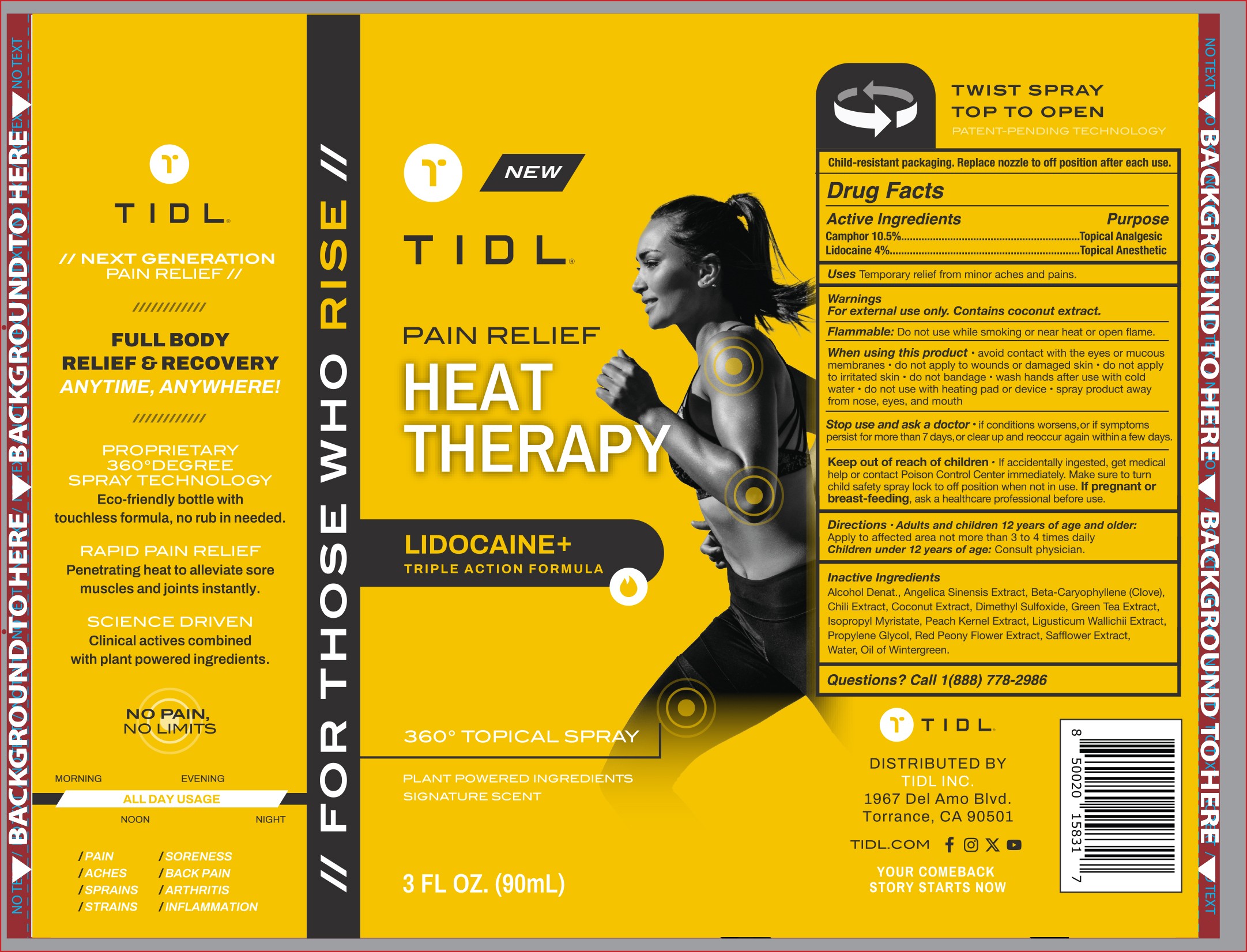 DRUG LABEL: TIDL PAIN RELIEF HEAT THERAPY Spray.
NDC: 84214-004 | Form: SPRAY
Manufacturer: Shenzhen Sam Technology Co., Ltd.
Category: otc | Type: HUMAN OTC DRUG LABEL
Date: 20240712

ACTIVE INGREDIENTS: LIDOCAINE 4 g/100 mL; CAMPHOR (NATURAL) 10.5 g/100 mL
INACTIVE INGREDIENTS: ALCOHOL; CARYOPHYLLENE; COCONUT; CAPSAICIN; LIGUSTICUM WALLICHII WHOLE; PROPYLENE GLYCOL; ISOPROPYL MYRISTATE; PAEONIA LACTIFLORA WHOLE; METHYL SALICYLATE; GREEN TEA LEAF; WATER; SAFFLOWER; DIMETHYL SULFOXIDE; PRUNUS PERSICA SEED; ANGELICA SINENSIS WHOLE

84214-004

Active Ingredient

Camphor 10.5%
Lidocaine 4%

Purpose

Topical Anesthetic

Use

Temporary relief from minor aches and pains.

Warnings

For external use only.Contains coconut extract.

Do not use

While smoking or near heat or open flame

When Using

·avoid contact with the eyes or mucous membranes
·do not apply to wounds or damaged skin
·do not apply to irritated skin
·do not bandage
·wash hands after use with cool water
·do not use with heating pad or device
·spray product away from nose,eyes,and mouth

Stop Use

if condition worsens, or if symptoms persist for more than 7 days, or clear up and reoccur again within a few days

Ask Doctor

if condition worsens, or if symptoms persist for more than 7 days, or clear up and reoccur again within a few days

Keep Oot Of Reach Of Children

If accidentally ingested get medical help or contact a Poison Control Center immediately. Make sure to turn child safety spray lock to off position when not in use. If pregnant or breast-feeding，ask a healthcare professional before use.

Directions

·Adults and children 12 years of age and older：Apply to affected area not more than 3 to 4 times daily
·Children under 12 years of age：Consult physician

Inactive ingredients

Alcohol Denat, Angelica Sinensis Extract, Beta-Caryophyllene（Clove), Chili Extract, Coconut Extract, Dimethyl Sulfoxide, Green Tea Extract，Isopropyl Myristate, Peach Kernel Extract, Ligusticum Wallichii Extract, Propylene Glycol, Red Peony Flower Extract, Safflower Extract, Water, Oil of Wintergreen.

Questions

Call 1(888) 778-2986